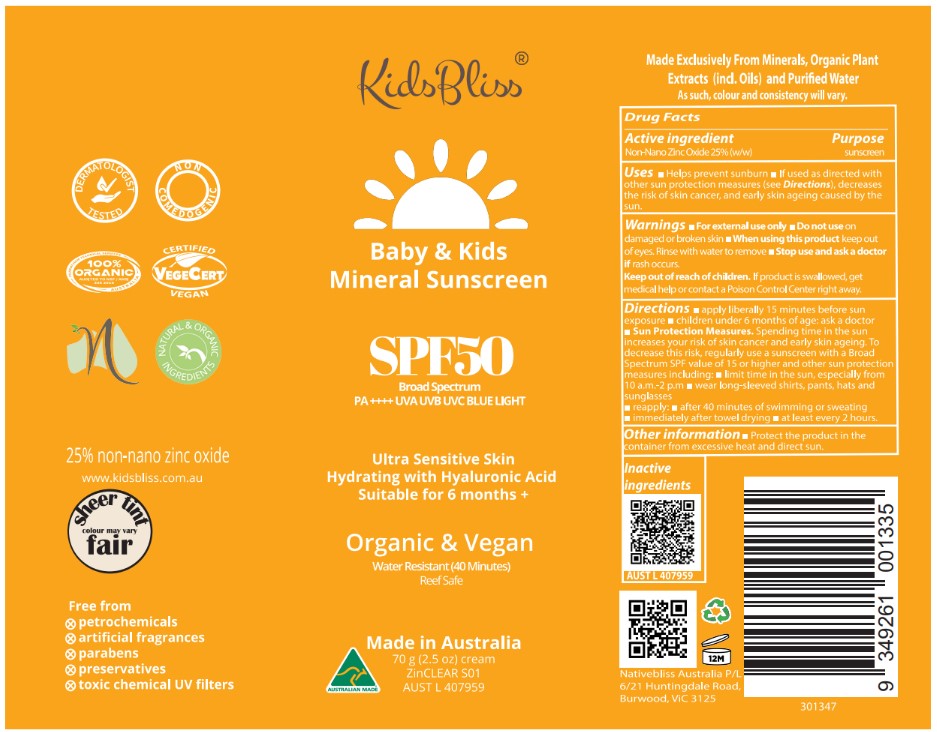 DRUG LABEL: KidsBliss Baby and Kids Mineral Sunscreen SPF50
NDC: 83252-089 | Form: CREAM
Manufacturer: VeganicSKN
Category: otc | Type: HUMAN OTC DRUG LABEL
Date: 20251024

ACTIVE INGREDIENTS: ZINC OXIDE 25 kg/100 kg
INACTIVE INGREDIENTS: SODIUM ASCORBATE; CALENDULA OFFICINALIS FLOWER; TOCOPHEROL; SIMMONDSIA CHINENSIS (JOJOBA) SEED OIL; XANTHAN GUM; CANDELILLA WAX; SODIUM HYALURONATE; POLYHYDROXYSTEARIC ACID (2300 MW); POTASSIUM CETYL PHOSPHATE; FERRIC OXIDE YELLOW; CITRUS PARADISI (GRAPEFRUIT) SEED OIL; CORIANDRUM SATIVUM (CORIANDER) SEED OIL; WATER; POLYGLYCERYL-3 RICINOLEATE; GLYCERIN; FERROSOFERRIC OXIDE; SODIUM CHLORIDE; HIPPOPHAE RHAMNOIDES SEED OIL; MALTODEXTRIN; .ALPHA.-BISABOLOL, (+/-)-; HELIANTHUS ANNUUS (SUNFLOWER) SEED OIL; ISOSTEARIC ACID; SODIUM HINOKITIOL; KAKADU PLUM; FERRIC OXIDE RED

KidsBliss Baby & Kids Mineral Sunscreen SPF50

Active ingredient: Zinc oxide 25% w/w

Purpose: sunscreen

INDICATIONS AND USAGE

Plese kindly refer to label

WARNINGS

For external use only.
Do not use on damaged r broken skin.
When using this product keep out of eyes. Rinse with water to remove. Stop use and ask a
doctor if rash occurs.
Keep out of reach of children.
If product is swallowed, get medical help or contact a Poison Control Center right away

Keep out of reach of childre

DOSAGE AND ADMINISTRATION

Please kindly refer to the label

INACTIVE INGREDIENT

Please kindly refer to the label